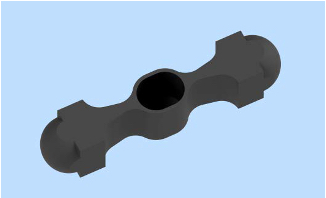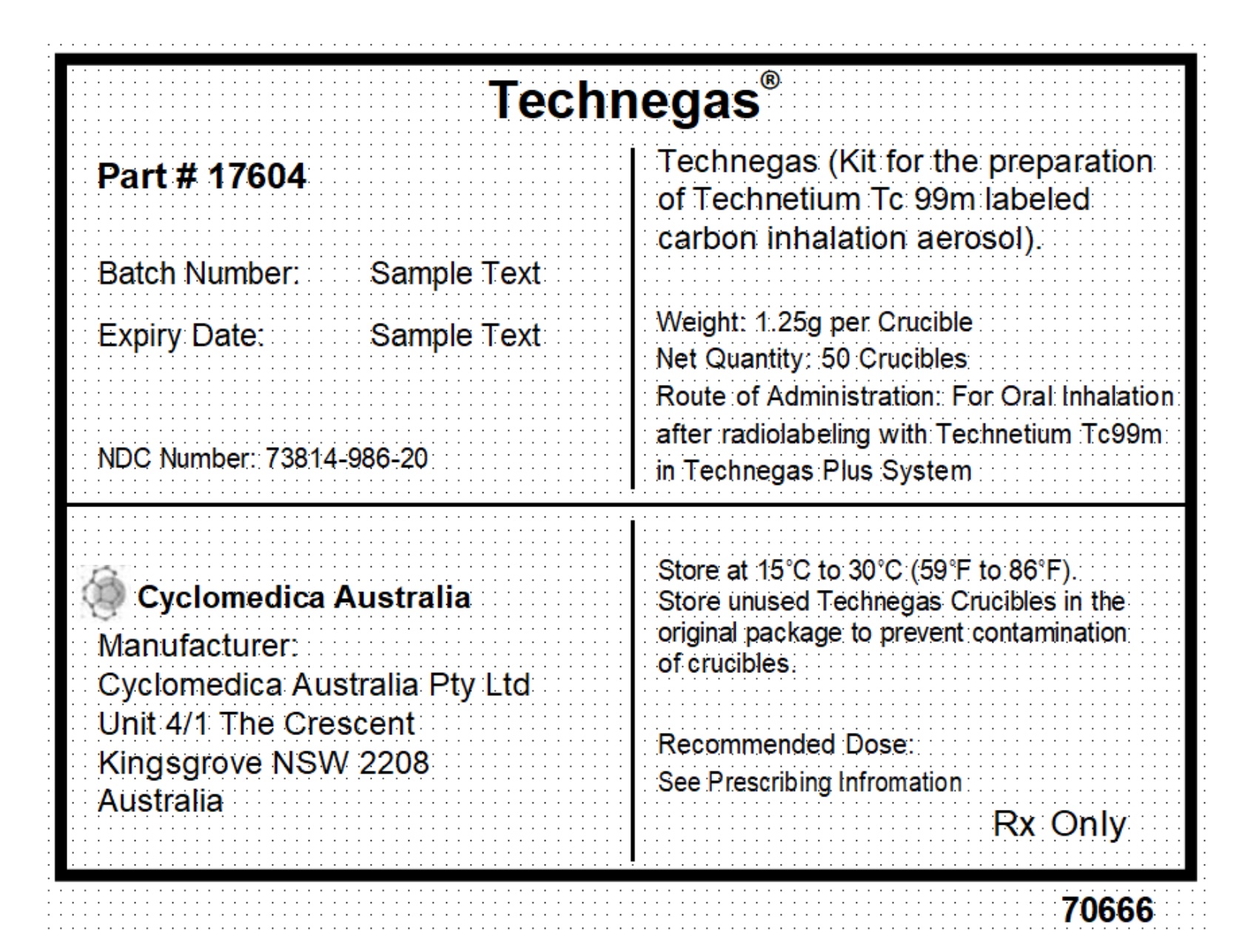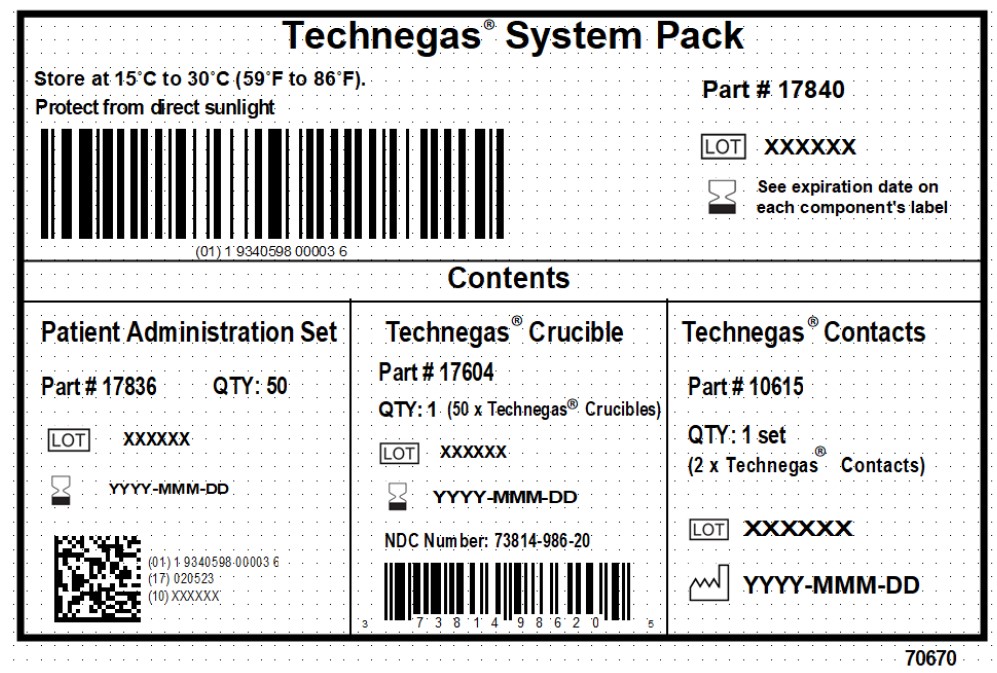 DRUG LABEL: TECHNEGAS
NDC: 73814-989 | Form: KIT | Route: RESPIRATORY (INHALATION)
Manufacturer: Cyclomedica Australia Pty Limited
Category: prescription | Type: HUMAN PRESCRIPTION DRUG LABEL
Date: 20260210

ACTIVE INGREDIENTS: GRAPHITE 1.25 g/1 1

HIGHLIGHTS OF PRESCRIBING INFORMATION

TECHNEGAS® (kit for the preparation of technetium Tc 99m- labeled carbon inhalation aerosol), for oral inhalation use.
These highlights do not include all the information needed to use TECHNEGAS safely and effectively. See full prescribing information for TECHNEGAS
Initial U.S. Approval: 2023

1 INDICATIONS AND USAGE

TECHNEGAS, when used with sodium pertechnetate Tc 99m in the Technegas Plus System, provides technetium Tc 99m-labeled carbon inhalation aerosol (Technegas Aerosol), a radioactive diagnostic agent for use in adults and pediatric patients aged 6 years and older for:

• visualizationofpulmonaryventilation
• evaluationofpulmonaryembolismwhenpairedwithperfusion imaging (1)

2 DOSAGE AND ADMINISTRATION

- For adult patients, the recommended activity of sodium pertechnetate Tc 99m injection to be loaded in the Technegas Crucible is 400 MBq to 1,000 MBq (10.8 mCi to 27 mCi) to achieve a lung count rate between 1,500 counts per second (cps) and 2,500 cps at the end of the last respiration. (2.2)
- For pediatric patients aged 6 years and older, a sufficient amount of Technegas Aerosol should be inhaled to achieve between 500 cps and 1,000 cps at the end of last respiration. The radioactivity to be loaded in the Technegas Crucible is a fraction of the recommended activity for adults adjusted by body weight. (2.2)
- Administer as soon as possible following preparation and complete inhalation within 10 minutes of preparation. (2.2)
- For drug handling, breathing techniques, preparation, and dosimetry information, see the full prescribing information. (2.1, 2.3, 2.4, 2.5)

3 DOSAGE FORMS AND STRENGTHS

TECHNEGAS (kit for the preparation of technetium Tc 99m labeled carbon inhalation aerosol) is a 1.25 gram single-use black to dark grey oval shaped graphite carbon crucible (Technegas Crucible). Upon addition of sodium pertechnetate Tc 99m injection, USP to the Technegas Crucible, the Technegas Plus System provides Technegas Aerosol for oral inhalation. (3)

4 CONTRAINDICATIONS

None (4)

5 WARNINGS AND PRECAUTIONS

Decreased Oxygen Saturation: Monitor oxygen saturation with continuous pulse oximetry. If clinically indicated, allow patients to breathe room air throughout the procedure and consider administration of supplemental oxygen before and at any time during the procedure. (5.1)
Radiation Exposure Risk: Ensure safe handling and preparation procedures to protect patients and health care providers from unintentional radiation exposure. (2.1, 5.2)

6 ADVERSE REACTIONS

The most common adverse reaction (≥ 1%) was hypoxia. (6.1)

To report SUSPECTED ADVERSE REACTIONS, contact Cyclomedica Australia Pty Ltd at toll free phone number 1-888-8-586-4396 or FDA at 1-800-FDA-1088 or www.fda.gov/medwatch.

8 USE IN SPECIFIC POPULATIONS

Lactation: Temporarily discontinue breastfeeding. A lactating woman should pump and discard breastmilk for at least 4 hours after Technegas Aerosol inhalation to minimize exposure to the breastfed infant. (8.2)

FULL PRESCRIBING INFORMATION

1 INDICATIONS AND USAGE

TECHNEGAS, when used with sodium pertechnetate Tc 99m in the Technegas Plus System, provides technetium Tc 99m-labeled carbon inhalation aerosol (Technegas Aerosol), for use in adults and pediatric patients aged 6 years and older for:

• visualization of pulmonary ventilation
• evaluation of pulmonary embolism when paired with perfusion imaging

2 DOSAGE AND ADMINISTRATION

2.1 Radiation Safety-Drug Handling

Handle Technegas Aerosol with appropriate safety measures to minimize radiation exposure to the patient and healthcare providers. During preparation and handling, use waterproof gloves and effective shielding [see Warnings and Precautions (5.2)].

Radiopharmaceuticals should be used by or under the control of healthcare providers who are qualified by specific training and experience in the safe use and handling of radionuclides, and whose experience and training have been approved by the appropriate governmental agency authorized to license the use of radionuclides.

2.2 Recommended Dose

The activity present in the lungs after each inhalation varies. Follow the pulmonary count rate during oral inhalation of Technegas Aerosol, using a gamma camera equipped with a standard collimator (low energy, low/medium resolution).

For adult patients, the recommended activity of sodium pertechnetate Tc 99m injection to be loaded in the Technegas Crucible is 400 MBq to 1,000 MBq (10.8 mCi to 27 mCi) to achieve a lung count rate between 1,500 counts per second (cps) and 2,500 cps at the end of the last respiration. Discontinue Technegas Aerosol administration at that point.

For pediatric patients aged 6 years and older, a sufficient amount of Technegas Aerosol should be inhaled until a lung count rate is obtained between 500 cps and 1,000 cps at the end of last respiration. Discontinue administration at that point. The radioactivity to be loaded in the Technegas Crucible for pediatric patients aged 6 years and older is a fraction of the recommended activity for adults, and is adjusted by body weight as listed in Table 1.

Table 1. Crucible Loading Activity of Sodium Pertechnetate Tc 99m Injection for Pediatric Patients Aged 6 Years and Older
Weight (kg) | Crucible Loading Activity MBq (mCi)
10 | 133 (3.6)
12 | 154 (4.2)
14 | 175 (4.7)
16 | 196 (5.3)
18 | 217 (5.9)
20 | 238 (6.4)
22 | 259 (7)
24 | 270 (7.6)
26 | 301 (8.1)
28 | 315 (8.5)
30 | 336 (9.1)
32 | 357 (9.7)
34 | 378 (10)
36 | 392 (11)
38 | 413 (11)
40 | 434 (12)
42 | 448 (12)
44 | 469 (13)
46 | 490 (13)
48 | 504 (14)
50 | 525 (14)
52-54 | 553 (15)
56-58 | 588 (16)
60-62 | 623 (17)
64-66 | 658 (18)
68 | 686 (19)

2.3 Administration Instructions

Administer Technegas Aerosol by oral inhalation using an FDA-cleared radionuclide rebreathing system for Technegas Aerosol (e.g., Patient Administration Set from Cyclomedica) that connects directly to the Technegas Plus System (TP) as soon as possible following preparation and complete inhalation within 10 minutes of preparation.

Monitor oxygen saturation level in patients with an oximeter [see Warnings and Precautions (5.1)]. Be prepared to allow patients to breathe room air during administration. Do not detach the patient administration set (PAS) from the patient to prevent residual aerosol from being released.

Prepare the patient in the imaging room or a preparation room before preparing Technegas Aerosol. For complete instructions on patient preparation, breathing techniques, and operation of the TP during administration, see the User Manual for the TP.

To facilitate uniform delivery of the aerosol from the apex-to-base of the lungs, perform the administration with the patient in the supine position.

Recommended Breathing Method

- For adult patients, the recommended breathing method to inhale the aerosol is through the mouthpiece by slow deep breathing from the residual functional capacity (end of calm expiration), followed by a 5-second breath-hold.
- For patients unable to hold their breath, normal breathing with deep inhalations without breath- holding can be used.
- For pediatric patients aged 6 years and older, instruct the patient to inhale the aerosol through the mouthpiece or inhalation line by normal breathing with deep inhalations without breath- holding.

When the adequate pulmonary counts are achieved for imaging, the patient must continue exhaling air through the filter equipped exhalation circuit of the PAS for five breaths to six breaths to trap residual aerosol being exhaled.

The PAS is single use only and should be disposed of as radioactive waste.

2.4 Preparation of Technegas Aerosol

Important Preparation Information

- Prepare Technegas Aerosol in the Technegas Plus System (TP) using the supplied Technegas Crucible. See the User Manual for a comprehensive description of the setup, operation, and maintenance of the TP.
- Use Sodium Pertechnetate Tc 99m Injection, USP obtained from a commercially available technetium Tc 99m generator.
- Only use ultra high purity (> 99.997% purity with less than 3 ppm oxygen) argon gas. The presence of oxygen in argon gas during the process of formation of Technegas Aerosol may lead to formation of Pertechnegas Aerosol (instead of Technegas Aerosol), which may affect the image quality.
- Wear protective gloves, aprons, and masks for radiation protection and infection control.
- Handle Technegas Crucibles with forceps. Any oil from the skin will reduce connection efficiency and Technegas yield.
- Prepare Technegas Aerosol using the TP at 15° to 30oC (59° to 86oF) in a ventilated area that is suitable for using radioactive materials (e.g., Nuclear Medicine Department) near the patient, to enable timely (within 10 minutes) administration [see Dosage and Administration (2.3)].
- The maximum use period for the TP is one year or 500 burn cycles, whichever occurs first. After this period, ask Cyclomedica to perform maintenance and recertify the TP for use.

Preparation:

1. Using forceps, remove a Technegas Crucible from its blister pack, inspect the crucible to ensure that it is free of chips or cracks, and place it on a clean flat surface. Store unused crucibles in the original packaging.
  (Note: When a blister pack of 10 crucibles is used for the first time, remove the tamper-proof seal to facilitate access to the crucibles. Then carefully remove one crucible (for preparation of each patient’s dose) from the blister pack and reinsert the cardboard backing material to cover all remaining crucibles in their respective individual blister pockets. This prevents ingress of any contaminating material from the immediate environment and allows the crucibles to be securely stored).
2. Prepare the Alcohol, USP (i.e.,95%ethanol) wetted crucible. Using a 1mL syringe, fill the crucible reservoir (approximately 0.1 mL) with Alcohol and then draw it back in the syringe.
3. Open the Technegas Plus System drawer and install the Alcohol wetted crucible between the support electrodes using forceps (see the Technegas Plus System User Manual for details on installation of the Technegas Crucible).
4. Rotate the crucible to ensure that good electrical contact is made with the support electrodes (Technegas Contacts); ensure the crucible reservoir is upright.
5. For adult patients, using a 1mL syringe with needle, load 400MBq to 1,000MBq (10.8mCito 27 mCi) of Sodium Pertechnetate Tc99m Injection, USP, in a volume of 0.1 mL while ensuring that the liquid meniscus does not exceed the height of the Crucible (the maximum crucible volume is 0.12 mL, and adding excess volume can lead to radioactive spill in the TP and may lead to formation of aerosol of free pertechnetate Tc 99m that may deteriorate image quality). For the recommended loading activity of Sodium Pertechnetate Tc 99m Injection in pediatric patients aged 6 years and older, refer to Table 1 [see Dosage and Administration (2.2)].
6. Close the drawer and run the SIMMER heating cycle to evaporate the liquid fromthecrucible reservoir. The process continues for 6 minutes, leaving a dry white residue of sodium pertechnetate Tc 99m and sodium chloride in the crucible. During this time the TP chamber is also completely filled with the argon gas (note: 100% argon atmosphere is necessary to prepare pure Technegas Aerosol). When the simmer is complete, the display will read: PRESS [START] TO INITIATE BURN.
7. Run the BURN heating cycle, during which the crucible containing the dry residue of sodium chloride and pertechnetate Tc 99m is heated to 2,750°C (4,982°F) for 15 seconds in TP, to produce Technegas Aerosol. At the end of BURN cycle, the display will change to “DISCONNECT THE MAINS PLEASE”.
  (Note: At this time the argon gas supply is turned OFF and the argon gas line can be disconnected. The main power on the TP can be switched OFF. The TP will remain powered ON from an internal battery for Technegas Aerosol administration to the patient. The TP may be moved to the patient as required.)
8. Administer Technegas Aerosol as soon as possible following preparation and completethe inhalation within 10 minutes of its preparation. Do not use after 10 minutes of preparation. [See the TP User Manual for connecting the PAS to the patient and to the TP.]
9. The crucible is single use only. The TP breaks the crucible at the end of Technegas Aerosol production to prevent re-use. Crucible fragments are radioactive and should be disposed appropriately. Refer to the Technegas Plus System User Manual for detailed information.

2.5 Radiation Dosimetry

The estimated radiation absorbed doses to various organs are shown in Table 2. The dose limiting organ is the lungs at 0.11 mGy/MBq.

The effective dose resulting from an estimated inhaled activity of 40 MBq (1.08 mCi) in adults is 0.6 mSv. The effective dose in a 10-year old pediatric patient from estimated inhaled activity of 15 MBq (0.41 mCi) is 0.47 mSv.

Table 2. Estimated Radiation Absorbed Dose from Inhalation of Technegas Aerosol
Organ | Absorbed Dose per Unit Activity Administered (mGy/MBq)
 | Adult | 15 Years | 10 Years | 5 Years**
Adrenals | 0.0068 | 0.00911 | 0.013 | 0.02
Bone surfaces | 0.0049 | 0.0063 | 0.0088 | 0.014
Brain | 0.00025 | 0.00033 | 0.00058 | 0.00094
Breast | 0.0067 | 0.0073 | 0.013 | 0.019
Gallbladder wall | 0.0023 | 0.0032 | 0.0055 | 0.0084
Gastrointestinal tract
Stomach wall | 0.0044 | 0.0062 | 0.0088 | 0.013
Small intestines wall | 0.00087 | 0.0013 | 0.0022 | 0.0039
Colon wall | 0.0014 | 0.0019 | 0.0034 | 0.0059
Upper large intestines wall | 0.0019 | 0.0025 | 0.0046 | 0.0077
Lower large intestines wall | 0.00074 | 0.001 | 0.0018 | 0.0018
Heart wall | 0.013 | 0.017 | 0.023 | 0.032
Kidneys | 0.002 | 0.003 | 0.0046 | 0.0072
Liver | 0.0057 | 0.0078 | 0.01 | 0.015
Lungs | 0.11 | 0.16 | 0.22 | 0.33
Muscles | 0.0028 | 0.0036 | 0.0049 | 0.0073
Esophagus | 0.0082 | 0.01 | 0.015 | 0.019
Ovaries | 0.00041 | 0.00055 | 0.0011 | 0.002
Pancreas | 0.0052 | 0.0073 | 0.01 | 0.016
Red marrow | 0.0033 | 0.0038 | 0.005 | 0.0066
Salivary glands | 0.0028 | 0.0036 | 0.0063 | 0.0098
Skin | 0.0012 | 0.0013 | 0.0022 | 0.0033
Spleen | 0.0048 | 0.0063 | 0.0093 | 0.015
Testes | 0.000061 | 0.000091 | 0.0002 | 0.00033
Thymus | 0.0082 | 0.01 | 0.015 | 0.019
Thyroid | 0.0029 | 0.0039 | 0.0069 | 0.011
Urinary bladder wall | 0.00032 | 0.00045 | 0.00074 | 0.0012
Uterus | 0.0003 | 0.00046 | 0.00083 | 0.0016
Remaining organs | 0.0027 | 0.0035 | 0.0047 | 0.0068
Effective dose (mSv/MBq) | 0.015 | 0.022 | 0.031 | 0.047

**Technegas Aerosol is not approved for pediatric patients younger than 6 years old [see Indications and Usage (1)].

3 DOSAGE FORMS AND STRENGTHS

Technegas (kit for the preparation of technetium Tc 99m-labeled carbon inhalation aerosol) is a 1.25 gram single-use dark grey to black small oval graphite carbon crucible (Technegas Crucible). Upon addition of sodium pertechnetate Tc 99m injection, USP to the Technegas Crucible, the Technegas Plus System provides Technegas Aerosol in argon gas.

4 CONTRAINDICATIONS

None.

5 WARNINGS AND PRECAUTIONS

5.1 Decreased Oxygen Saturation

Decrease in oxygen saturation may occur during or after the inhalation of Technegas Aerosol. Oxygen saturation nadirs as low as 60% have been reported in a published study [see Adverse Reactions (6.1)]. In an efficacy trial, 79% of patients received supplemental oxygen or had the flow of Technegas Aerosol interrupted. Patients with compromised respiratory function may be at increased risk for decreased oxygen saturation. Monitor oxygen saturation with continuous pulse oximetry. If clinically indicated, allow patients to breathe room air throughout the procedure and consider administration of supplemental oxygen before and at any time during the procedure.

5.2 Radiation Exposure Risk

Technegas Aerosol contributes to a patient’s overall long-term cumulative radiation exposure. Long-term cumulative radiation exposure is associated with an increased risk of cancer. Ensure safe handling and preparation procedures to protect patients and health care providers from unintentional radiation exposure.

5.3 Bronchospasm

As with other inhaled aerosol medications, Technegas Aerosol may result in acute bronchoconstriction, especially in patients with heightened bronchoreactivity, such as patients with asthma or other lung or allergic disorders. Monitor all patients for bronchospasm.

6 ADVERSE REACTIONS

The following clinically significant adverse reactions are described elsewhere in the labeling:

- Decreased Oxygen Saturation [see Warnings and Precautions (5.1)]

6.1 Clinical Trial Experience

Because clinical trials are conducted under widely varying conditions, adverse reaction rates observed in the clinical trials of a drug cannot be directly compared to rates in the clinical trials of another drug and may not reflect the rates observed in clinical practice.

The safety of Technegas Aerosol was evaluated in 291 patients undergoing ventilation studies with prospective data collection. Patients received an amount of Technegas Aerosol to achieve 1,500 cps to 2,500 cps by oral inhalation. The mean age of patients was 60 years (range:18 to 95 years); distribution by race was 92 % White, 7% Black or African American, 0.3 % Asian, and 0.3 % unreported; and distribution by ethnicity was 4% Hispanic/Latino and 96 % non-Hispanic/Latino.

Adverse reactions were reported in 10 patients (3.4%). The adverse reaction occurring at ≥ 1% in patients receiving Technegas Aerosol was hypoxia (1%).

Adverse reactions reported at < 1% were dizziness, dysgeusia, cough, dyspnea [not otherwise specified], throat irritation, and upper respiratory tract congestion.

In one published study, oxygen saturation was monitored in a series of patients undergoing Technegas Aerosol ventilation scintigraphy for suspected pulmonary embolism (n=28) or pulmonary disease (n=10). Of these 38 patients without pre-oxygenation, oxygen saturation fell to < 90% in 26 (68%) patients and < 85% in 15 (39%) patients. The recorded lowest value for each patient was usually observed after the first or second inhalation.

8 USE IN SPECIFIC POPULATIONS

8.1 Pregnancy

Risk Summary

Available data with Technegas Aerosol use in pregnant women from several small retrospective studies are insufficient to evaluate for a drug associated risk for major birth defects, miscarriage, or other adverse maternal or fetal outcomes. The radiation dose to the fetus after inhalation of Technegas Aerosol has ranged from 0.007 mGy to 0.14 mGy (see Data). Animal reproduction studies have not been conducted with Technegas Aerosol. However, all radiopharmaceuticals, including Technegas Aerosol have the potential to cause fetal harm depending on the fetal stage of development and the magnitude of the radiation dose. If considering Technetium Aerosol administration to a pregnant woman, inform the patient of the potential for adverse pregnancy outcomes based on the radiation dose from Technetium Aerosol and the gestational timing of exposure.

The background risk of major birth defects and miscarriage for the indicated population is unknown. All pregnancies have a background risk of birth defect, loss, or other adverse outcomes. In the U.S. general population, the estimated background risks of major birth defects and miscarriage in clinically recognized pregnancies are 2% to 4% and 15% to 20%, respectively.

Data

Human Data

The radiation dose to the fetus after inhalation of Technegas Aerosol was calculated according to the stage of gestation, ranging from 0.007 mGy at the early stage through 3-months of gestation up to 0.011 mGy to 0.14 mGy at 6-months and 9-months of gestation, respectively. No adverse fetal effects or radiation-related risks have been identified for diagnostic procedures involving less than 50 mGy, which represents less than 10 mGy fetal doses.

8.2 Lactation

Risk Summary
There are no data on the presence of Technegas Aerosol in human milk, the effects of Technegas Aerosol on the breastfed infant, or the effects on milk production. Published case reports describe the presence of technetium-99 in human milk. Based on clinical guidelines, exposure of Technetium Aerosol to a breast fed infant may be minimized by advising a lactating woman to pump and discard breast milk for a minimum of 4 hours after administration of Technegas Aerosol. The developmental and health benefits of breastfeeding should be considered along with the mother’s clinical need for Technegas Aerosol and any potential adverse effects on the breastfed child from Technegas Aerosol or from the underlying maternal condition.

8.4 Pediatric Use

The safety and effectiveness of Technegas Aerosol for lung ventilation imaging to visualize pulmonary ventilation and pulmonary embolism when paired with perfusion have been established in pediatric patients aged 6 years and older.

The safety and effectiveness of Technegas Aerosol with the patient administration set have not been established in pediatric patients less than 6 years of age.

8.5 Geriatric Use

Of the total number of patients receiving Technegas Aerosol in clinical studies for lung ventilation imaging, 122 (41.9 %) were 65 years of age and older, while 58 (20 %) were 75 years of age and older. No overall differences in safety or effectiveness were observed between these patients and younger patients, and other reported clinical experience has not identified differences in responses between elderly and younger patients.

11 DESCRIPTION

11.1 Chemical Characteristics

TECHNEGAS (kit for the preparation of technetium Tc 99m-labeled carbon inhalation aerosol) is a 1.25 gram black to dark grey graphite carbon crucible (Technegas Crucible). Graphite is a polymorph of the element carbon, appears opaque, and crystallizes in the hexagonal system. The crucible has the following appearance and physical dimensions:

Table 3. Physical Dimensions of Crucible
Length | 31.25 to 32.75 mm
Wall Thickness | 0.39 to 0.81 mm
Base Thickness | 0.34 to 0.81 mm
Maximum volume capacity | 0.12 mL

Technegas Crucible when used with sodium pertechnetate Tc 99m injection, USP in the Technegas Plus System (also commonly referred to as TechnegasPlus Technegas Generator or TP), provides technetium Tc 99m-labeled carbon inhalation aerosol in argon gas (Technegas Aerosol), a radioactive diagnostic agent for oral inhalation.

During the process of formation of technetium Tc 99m-labeled carbon inhalation aerosol, when dried pertechnetate Tc 99m in Technegas Crucible is heated to 2,750°C (4,982°F) for 15 seconds in the TP using the Alternate Current arc, both the technetium and a portion of the carbon crucible are volatilized. The reduction of pertechnetate Tc 99m results in elemental technetium Tc 99m that serves as a nucleation site for the condensing of the volatile carbon, producing hydrophobic particles made up of a technetium Tc 99m core surrounded by layers of carbon. More than 90% of the technetium Tc 99m activity is technetium Tc 99m-labeled carbon particles. More than 80% of technetium Tc 99m carbon aerosol particles are < 0.92 micrometer in size. The technetium Tc 99m carbon particles are suspended in argon gas as an aerosol for inhalation. The concentration of carbon labeled particles in argon depends on the amount of technetium Tc 99m used but is less than 98 mcg/liter in Technegas Crucible loading of 0.1ml of Sodium Pertechnetate Tc99m.

11.2 Physical Characteristics

Technetium-99m decays by isomeric transition with a physical half-life of 6 hours. The photon that is useful for imaging studies is listed in Table 4.

Table 4. Principal Radiation Emission Data for Technetium-99m
Radiation | Mean % per Disintegration | Mean Energy (keV)
Gamma-2 | 88.5 | 140.5

The specific gamma-ray constant for technetium Tc 99m is 5.23 m2·pGy·(MBq)−1·s−1 [0.795 cm2·R·(mCi)−1·h−1]. The first half-value thickness of lead for technetium-99m is 0.017 cm (Pb). A range of values for the relative attenuation of the radiation emitted by this radionuclide that results from the interposition of various thicknesses of lead is shown in Table 5. For example, the use of 3 mm thickness of lead will decrease the external radiation exposure by a factor of 1,000.

Table 5. Radiation Attenuation by Lead Shielding
Lead Shield Thickness (mm) | Coefficient of Attenuation
0.25 | 0.5
1 | 0.1
2 | 0.01
3 | 0.001
4 | 0.0001

To correct for physical decay of this radionuclide, the fractions that remain at selected time intervals after the time of calibration are shown in Table 6.

Table 6. Physical Decay Chart of Technetium-99m, Half Life: 6 Hours
Hours | Fraction Remaining | Hours | Fraction Remaining
0* | 1 | 7 | 0.447
1 | 0.891 | 8 | 0.398
2 | 0.794 | 9 | 0.355
3 | 0.708 | 10 | 0.316
4 | 0.631 | 11 | 0.282
5 | 0.562 | 12 | 0.251
6 | 0.501

*Calibration Time

12 CLINICAL PHARMACOLOGY

12.1 Mechanism of Action

When the Technegas Aerosol particles are inhaled, they are mechanically deposited on the epithelium of ventilated pulmonary bronchioles and alveoli. Localization of the aerosol is not mediated by specific pharmacologic receptors; rather the distribution is determined by the aerodynamic function of the lungs.

12.2 Pharmacodynamics

Technegas Aerosol has no known pharmacological effects.

12.3 Pharmacokinetics

Distribution

After inhalation, Technegas Aerosol is adsorbed on the walls of pulmonary bronchioles and alveoli. The distribution within the lungs is determined by the size and aerodynamic properties of the individual particles. Following inhalation, the particles are retained in the lung. The redistribution of Technegas Aerosol following inhalation to human subjects has been monitored for as long as 70 hours without evidence of particulate translocation.

Elimination
There is no intravascular clearance, and the elimination of radioactivity occurs by the physical decay of the Technetium-99m. The Technegas Aerosol particles that are deposited in the mouth and along the mucociliary elevator are cleared by swallowing or expectoration. The particles that deposit in the alveolar region are cleared by alveolar macrophages.

13 NONCLINICAL TOXICOLOGY

13.1 Carcinogenesis, Mutagenesis, Impairment of Fertility

No long-term animal studies have been performed to evaluate carcinogenic or mutagenic potential, or whether this drug affects fertility in males or females.

14. CLINICAL STUDIES

The safety and effectiveness of Technegas Aerosol were evaluated in two studies. Study 1 (NCT03054870) was a single-arm, fixed-sequence, prospective study comparing Technegas Aerosol and xenon Xe 133 ventilation imaging in 200 patients undergoing ventilation scintigraphy. Xenon Xe 133 imaging was performed first, followed by Technegas Aerosol imaging.

Mean patient age was 60 years (range: 20 years to 88 years) and 53% were male. Distribution by race was 89% White, 10% Black or African American, and 0.5% Asian; and distribution by ethnicity was 2% Hispanic/Latino and 98% non-Hispanic/Latino.

The images were interpreted in a randomized sequence by three independent readers blinded to clinical information. Each reader assessed six standardized lung regions for ventilation using a three- point scale. The study showed that the overall percent agreement between Technegas Aerosol and xenon Xe 133 ventilation scores on matched images exceeded the pre-specified threshold of 60%. The lower bounds of the 97.18% confidence interval (due to the reported interim analysis following O’Brien-Fleming boundary) were 72%, 66%, and 76% for readers 1, 2, and 3, respectively.

Study 2 was a prospective observational study in 100 patients with suspected acute pulmonary embolism (56% male, age range 50 years to 90 years). Each patient underwent technetium Tc 99m albumin aggregated (MAA) lung perfusion scintigraphy and Technegas Aerosol ventilation scintigraphy as well as reference standard imaging using computed tomographic pulmonary angiography (CTPA) within 24 hours. The observed percent agreement for the presence of pulmonary embolism between CTPA and Technegas Aerosol ventilation scintigraphy paired with perfusion scintigraphy was 95%.

16 HOW SUPPLIED/STORAGE AND HANDLING

How Supplied
TECHNEGAS (kit for the preparation of technetium Tc 99m-labeled carbon inhalation aerosol) is a 1.25 gram single-use black to dark grey oval shape graphite carbon crucible packaged into thermoformed blister packs. Each carton contains five blister packs of 10 single-use Technegas Crucibles (NDC 73814-986-20).

The following components are supplied separately by Cyclomedica for the preparation of Technegas Aerosol:

- Patient Administration Sets (PAS)
- Technegas Contacts (replacement electrodes) • Technegas Plus System

The following items are not supplied by Cyclomedica and are provided by the user:

- Sodium Pertechnetate Tc 99m Injection, USP
- Ultra-high purity (minimum 99.997% purity with less than 3 ppm of oxygen) argon gas
- Ethanol meeting requirements of Alcohol, USP.

Storage and Handling
Store Technegas Crucibles at 15°C to 30°C (59°F to 86° F). Store unused crucibles in the original package to prevent contamination of crucibles.

The Technegas Crucible and PAS are single use components. The crucible is split into pieces after use by the Technegas Plus System to prevent its reuse. Dispose of the radioactive crucible pieces and PAS as radioactive waste in accordance with applicable regulations.

The maximum use period for the Technegas Plus System is one year or 500 burn cycles, whichever occurs first. After this period, ask Cyclomedica to perform maintenance and recertify the Technegas Plus System for use.

This radiopharmaceutical is approved for use by persons under license by the Nuclear Regulatory Commission or the relevant regulatory authority of an Agreement State.

17 PATIENT COUNSELING INFORMATION

Pregnancy
Advise pregnant women of the risk of fetal exposure to radiation from a Technegas Aerosol ventilation imaging procedure [see Use in Specific Populations (8.1)].

Lactation:
Advise lactating women that pumping and discarding breast milk for a minimum of 4 hours after Technegas Aerosol administration may minimize exposure in the breastfed infant [see Use in Specific Populations (8.2)].

TECHNEGAS®

(kit for the preparation of technetium Tc 99m- labeled carbon inhalation aerosol), for oral inhalation use Initial U.S. Approval: 2023